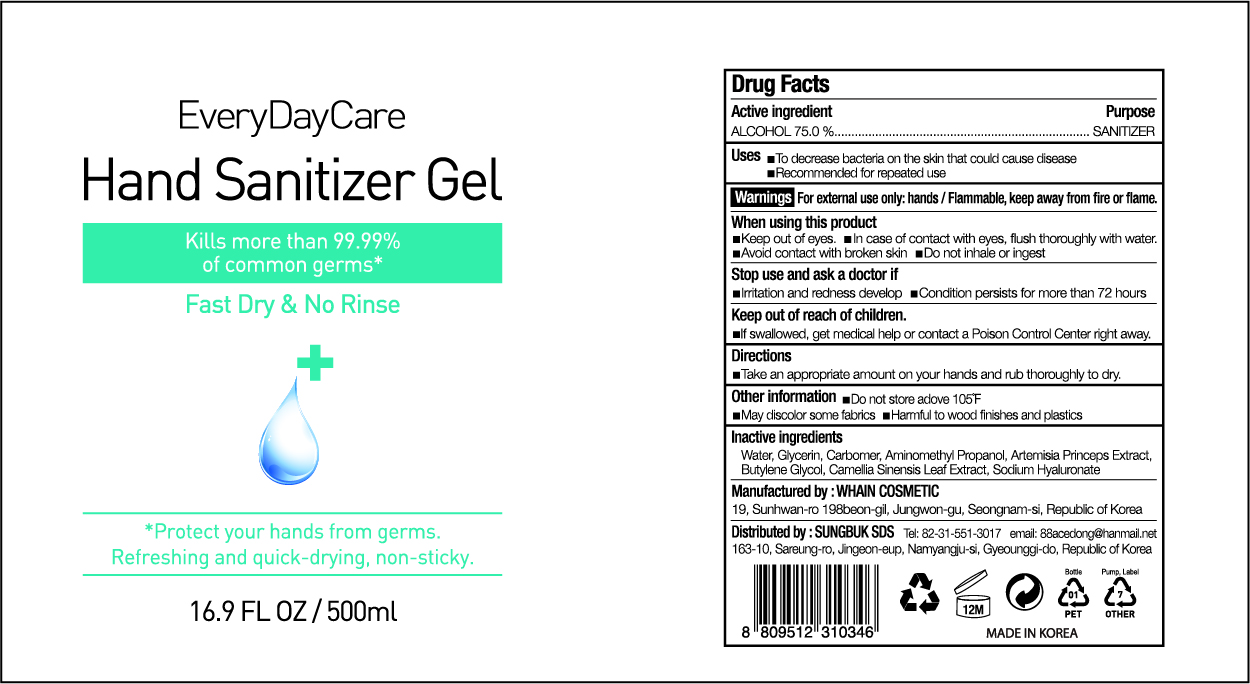 DRUG LABEL: EveryDayCare Hand Sanitizer Gel
NDC: 73823-755 | Form: GEL
Manufacturer: WHAIN COSMETIC
Category: otc | Type: HUMAN OTC DRUG LABEL
Date: 20200512

ACTIVE INGREDIENTS: ALCOHOL 375 mL/500 mL
INACTIVE INGREDIENTS: AMINOMETHYL PROPANEDIOL; GLYCERIN; HYALURONATE SODIUM; BUTYLENE GLYCOL; CARBOMER HOMOPOLYMER, UNSPECIFIED TYPE; WATER; ARTEMISIA PRINCEPS LEAF; GREEN TEA LEAF

EveryDayCare Hand Sanitizer Gel
500 ml : 73823-755-01